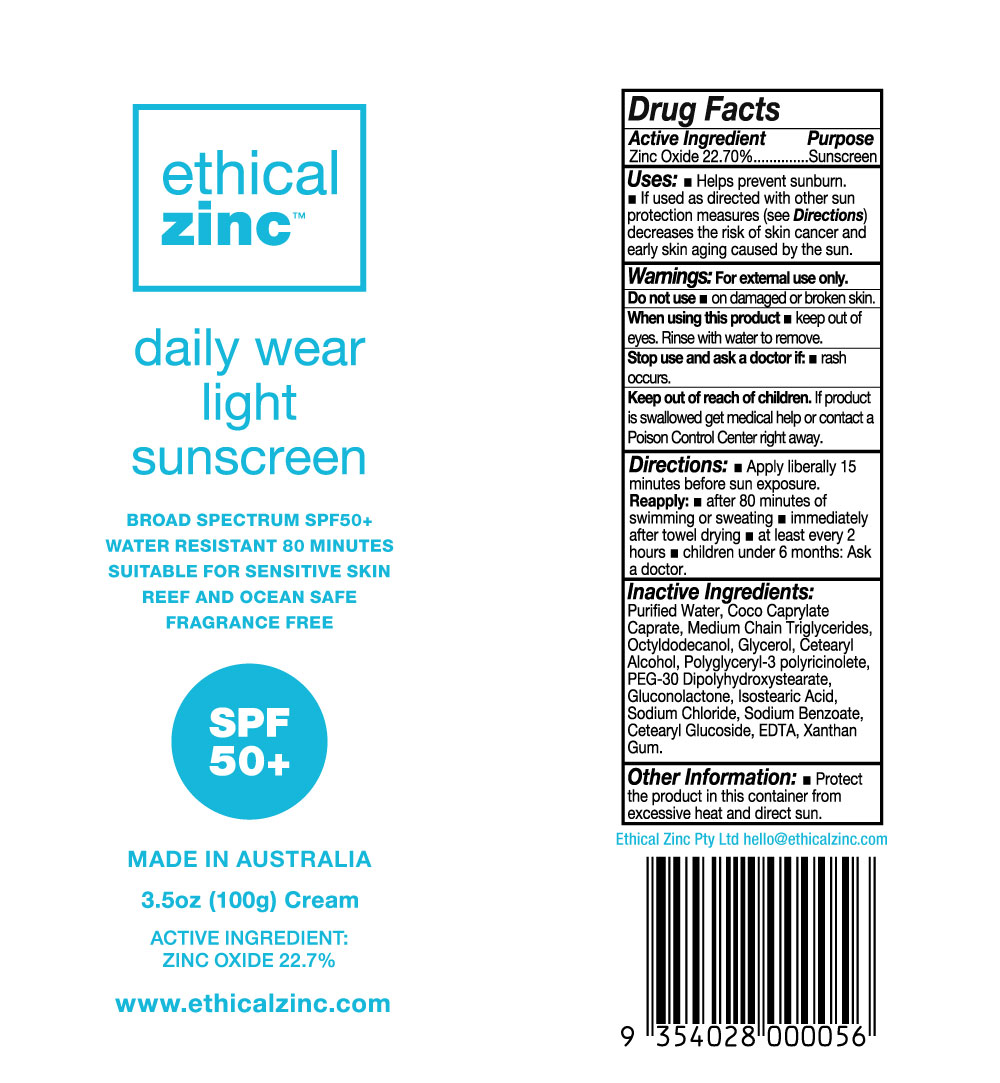 DRUG LABEL: ETHICAL ZINC DAILY WEAR LIGHT SUNSCREEN


NDC: 72962-102 | Form: LOTION
Manufacturer: ETHICAL ZINC PTY LTD
Category: otc | Type: HUMAN OTC DRUG LABEL
Date: 20230925

ACTIVE INGREDIENTS: ZINC OXIDE 22.7 g/100 g
INACTIVE INGREDIENTS: WATER; COCO-CAPRYLATE/CAPRATE; MEDIUM-CHAIN TRIGLYCERIDES; OCTYLDODECANOL; GLYCERIN; CETOSTEARYL ALCOHOL; POLYGLYCERYL-3 RICINOLEATE; PEG-30 DIPOLYHYDROXYSTEARATE; GLUCONOLACTONE; ISOSTEARIC ACID; SODIUM CHLORIDE; SODIUM BENZOATE; CETEARYL GLUCOSIDE; EDETIC ACID; XANTHAN GUM

ETHICAL ZINC - DAILY WEAR LIGHT SUNSCREEN SPF-50+ (72962-102)

ACTIVE INGREDIENTS

ZINC OXIDE 22.70%

PURPOSE

SUNSCREEN

USE

- HELPS PREVENT SUNBURN.
- IF USED AS DIRECTED WITH OTHER SUN PROTECTION MEASURES (SEE DIRECTIONS) DECREASES THE RISK OF CANCER AND EARLY SKIN AGING CAUSED BY THE SUN.

WARNINGS

FOR EXTERNAL USE ONLY.

DO NOT USE

- ON DAMAGED OR BROKEN SKIN.

WHEN USING THIS PRODUCT

- KEEP OUT OF EYES. RINSE WITH WATER TO REMOVE.

STOP USE AND ASK A DOCTOR IF

- RASH OCCURS.

KEEP OUT OF REACH OF CHILDREN. IF PRODUCT IS SWALLOWED, GET MEDICAL HELP OR CONTACT A POISON CONTROL CENTER RIGHT AWAY.

DIRECTIONS

- APPLY LIBERALLY 15 MINUTES BEFORE SUN EXPOSURE.

REAPPLY:

- AFTER 80 MINUTES OF SWIMMING OR SWEATING
- IMMEDIATELY AFTER TOWEL DRYING
- AT LEAST EVERY 2 HOURS
- CHILDREN UNDER 6 MONTHS: ASK A DOCTOR.

INACTIVE INGREDIENTS

PURIFIED WATER, COCO CAPRYLATE/CAPRATE, MEDIUM CHAIN TRIGLYCERIDES, OCTYLDODECANOL, GLYCEROL, CETEARYL ALCOHOL, POLYGLYCERYL-3 POLYRICINOLEATE, PEG-30 DIPOLYHYDROXYSTEARATE, GLUCONOLACTONE, ISOSTEARIC ACID, SODIUM CHLORIDE, SODIUM BENZOATE, CETEARYL GLUCOSIDE, EDTA, XANTHAN GUM.

OTHER INFORMATION

- PROTECT THE PRODUCT IN THIS CONTAINER FROM EXCESSIVE HEAT AND DIRECT SUN.